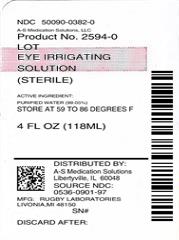 DRUG LABEL: Eye Irrigating
NDC: 50090-0382 | Form: SOLUTION
Manufacturer: A-S Medication Solutions
Category: otc | Type: HUMAN OTC DRUG LABEL
Date: 20170927

ACTIVE INGREDIENTS: WATER 99.05 mL/100 mL
INACTIVE INGREDIENTS: BORIC ACID; SODIUM BORATE; SODIUM CHLORIDE; HYDROCHLORIC ACID; SODIUM HYDROXIDE; EDETATE DISODIUM; SORBIC ACID

Drug Facts

Active ingredient

Purified water 99.05%

Purpose

Eyewash

Uses

washes the eye to help relieve:

- irritation
- stinging
- itching
  by removing:
- loose foreign material
- air pollutants (smog or pollen)
- chlorinated water

Warnings

Do not use if solution changes color or becomes cloudy

When using this product

- remove contact lenses before use
- do not touch tip of container to any surface to avoid contamination
- replace cap after use

Stop use and ask a doctor if

- you experience eye pain, changes in vision, continued redness or irritation of the eye
- condition worsens or persists
- you have open wounds in or near the eye

Keep out of reach of children.

If swallowed, get medical help or contact a Poison Control Center right away.

Directions

- flush the affected eye(s) as needed
- control the rate of flow of solution by placing pressure on the bottle

When using an eye cup

- rinse the cup with clean water immediately before each use
- avoid contamination of the rim and inside surfaces of the cup
- fill the cup half full and apply the cup to the affected eye(s), pressing tightly to prevent the escape of the liquid
- tilt the head backward. Open eyelid wide and rotate eyeball to ensure thorough bathing with the wash
- rinse the cup with clean water after each use

Other information

- store at 15° - 30°C (59° - 86°F)
- keep tightly closed

Inactive ingredients

boric acid, sodium borate and sodium chloride. Hydrochloric acid and/or sodium hydroxide may be added to adjust pH. PRESERVATIVE ADDED: edetate disodium 0.025% and sorbic acid 0.1%.

Questions or comments?

1-800-645-2158

Serious side effects associated with use of this product may be reported to this number.

Distributed by:

Rugby Laboratories

31778 Enterprise Drive

Livonia, MI 48150

© Rugby Laboratories
REV. 04/13 R-115

Re-order No. 370044

6998603

AK07025

HOW SUPPLIED

Product: 50090-0382

NDC: 50090-0382-0 118 mL in a BOTTLE